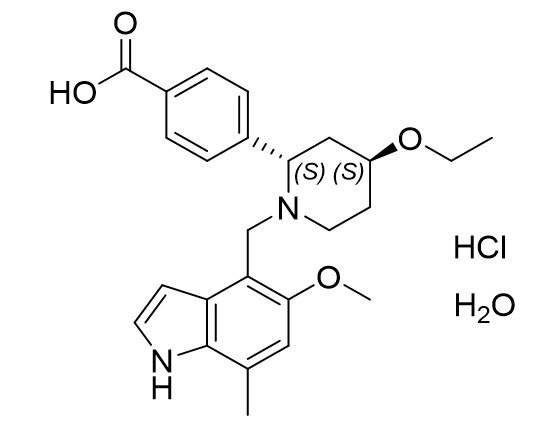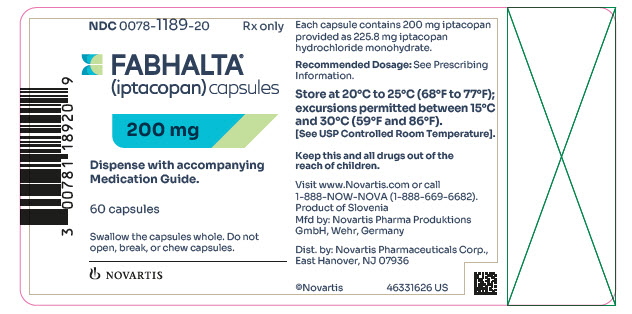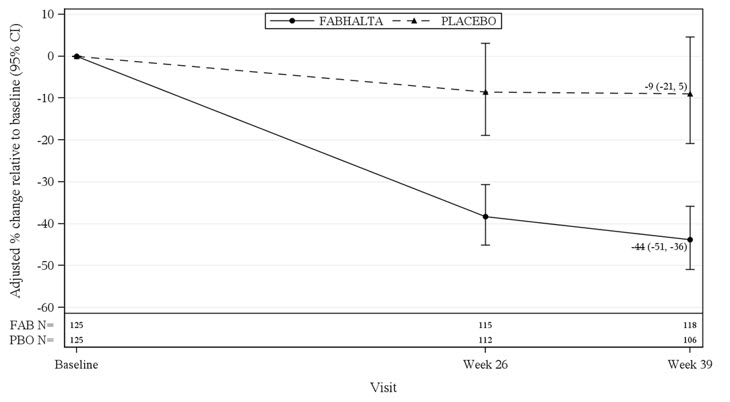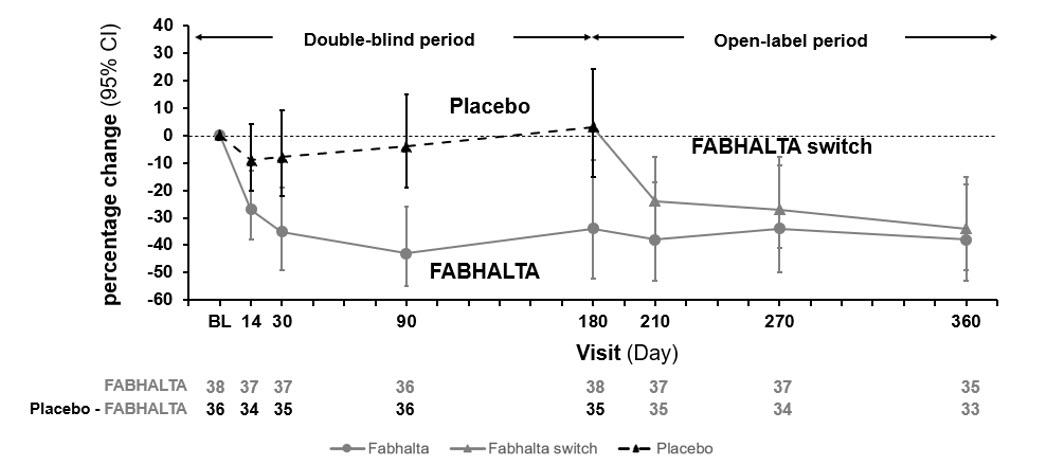 DRUG LABEL: FABHALTA
NDC: 0078-1189 | Form: CAPSULE
Manufacturer: Novartis Pharmaceuticals Corporation
Category: prescription | Type: HUMAN PRESCRIPTION DRUG LABEL
Date: 20250320

ACTIVE INGREDIENTS: IPTACOPAN HYDROCHLORIDE 200 mg/1 1
INACTIVE INGREDIENTS: FERROSOFERRIC OXIDE; GELATIN; POTASSIUM HYDROXIDE; PROPYLENE GLYCOL; FERRIC OXIDE RED; SHELLAC; AMMONIA; TITANIUM DIOXIDE; FERRIC OXIDE YELLOW

HIGHLIGHTS OF PRESCRIBING INFORMATION

These highlights do not include all the information needed to use FABHALTA safely and effectively. See full prescribing information for FABHALTA.
FABHALTA® (iptacopan) capsules, for oral use
Initial U.S. Approval: 2023

WARNING: SERIOUS INFECTIONS CAUSED BY ENCAPSULATED BACTERIA

See full prescribing information for complete boxed warning.

FABHALTA increases the risk of serious and life-threatening infections caused by encapsulated bacteria, including Streptococcus pneumoniae, Neisseria meningitidis, and Haemophilus influenzae type b.

- Complete or update vaccination for encapsulated bacteria at least 2 weeks prior to the first dose of FABHALTA, unless the risks of delaying FABHALTA outweigh the risk of developing a serious infection. Comply with the most current Advisory Committee on Immunization Practices (ACIP) recommendations for vaccinations against encapsulated bacteria in patients receiving a complement inhibitor. (5.1)
- Patients receiving FABHALTA are at increased risk for invasive disease caused by encapsulated bacteria, even if they develop antibodies following vaccination. Monitor patients for early signs and symptoms of serious infections and evaluate immediately if infection is suspected. (5.1)

FABHALTA is available only through a restricted program under a Risk Evaluation and Mitigation Strategy (REMS) called FABHALTA REMS. (5.2)

RECENT MAJOR CHANGES

Indications and Usage (1.2) | 8/2024
Indications and Usage (1.3) | 3/2025
Dosage and Administration (2.1) | 3/2024

1 INDICATIONS AND USAGE

FABHALTA is a complement factor B inhibitor, indicated for:

- the treatment of adults with paroxysmal nocturnal hemoglobinuria (PNH). (1.1)
- the reduction of proteinuria in adults with primary immunoglobulin A nephropathy (IgAN) at risk of rapid disease progression, generally a urine protein-to-creatinine ratio (UPCR) ≥ 1.5 g/g. (1.2)
  This indication is approved under accelerated approval based on reduction of proteinuria. It has not been established whether FABHALTA slows kidney function decline in patients with IgAN.
  Continued approval for this indication may be contingent upon verification and description of clinical benefit in a confirmatory clinical trial.
- the treatment of adults with complement 3 glomerulopathy (C3G), to reduce proteinuria. (1.3)

2 DOSAGE AND ADMINISTRATION

200 mg orally twice daily with or without food. (2.2)

3 DOSAGE FORMS AND STRENGTHS

Capsules: 200 mg (3)

4 CONTRAINDICATIONS

- Serious hypersensitivity to iptacopan or any of the excipients. (4)
- Initiation in patients with unresolved serious infection caused by encapsulated bacteria. (4)

5 WARNINGS AND PRECAUTIONS

- Monitoring of PNH Manifestations After FABHALTA Discontinuation: Monitor for signs of hemolysis after discontinuation. (5.3)
- Hyperlipidemia: Monitor serum lipid parameters periodically during treatment and initiate cholesterol-lowering medication, if indicated. (5.4)

6 ADVERSE REACTIONS

- Most common adverse reactions in adults with PNH (incidence ≥ 10%) were headache, nasopharyngitis, diarrhea, abdominal pain, bacterial infection, viral infection, nausea and rash. (6.1)
- Most common adverse reactions in adults with IgAN (incidence ≥ 5%) were upper respiratory tract infection, lipid disorder, and abdominal pain. (6.1)
- Most common adverse reactions in adults with C3G (incidence ≥ 10%) were nasopharyngitis and viral infections. (6.1)

To report SUSPECTED ADVERSE REACTIONS, contact Novartis Pharmaceuticals Corporation at 1-888-669-6682 or FDA at 1-800-FDA-1088 or www.fda.gov/medwatch.

7 DRUG INTERACTIONS

- CYP2C8 inducers (e.g., rifampin): May decrease iptacopan exposure. Monitor for loss of efficacy. (7.1)
- Strong CYP2C8 inhibitors (e.g., gemfibrozil): May increase iptacopan exposure. Coadministration not recommended. (7.2)

8 USE IN SPECIFIC POPULATIONS

- Severe hepatic impairment: Use not recommended. (8.7)

FULL PRESCRIBING INFORMATION

WARNING: SERIOUS INFECTIONS CAUSED BY ENCAPSULATED BACTERIA

FABHALTA, a complement inhibitor, increases the risk of serious infections, especially those caused by encapsulated bacteria, such as Streptococcus pneumoniae, Neisseria meningitidis, and Haemophilus influenzae type b [see Warnings and Precautions (5.1)]. Life-threatening and fatal infections with encapsulated bacteria have occurred in patients treated with complement inhibitors. These infections may become rapidly life-threatening or fatal if not recognized and treated early.

- Complete or update vaccination for encapsulated bacteria at least 2 weeks prior to the first dose of FABHALTA, unless the risks of delaying therapy with FABHALTA outweigh the risk of developing a serious infection. Comply with the most current Advisory Committee on Immunization Practices (ACIP) recommendations for vaccinations against encapsulated bacteria in patients receiving a complement inhibitor. See Warnings and Precautions (5.1) for additional guidance on the management of the risk of serious infections caused by encapsulated bacteria.
- Patients receiving FABHALTA are at increased risk for invasive disease caused by encapsulated bacteria, even if they develop antibodies following vaccination. Monitor patients for early signs and symptoms of serious infections and evaluate immediately if infection is suspected.

Because of the risk of serious infections caused by encapsulated bacteria, FABHALTA is available only through a restricted program under a Risk Evaluation and Mitigation Strategy (REMS) called the FABHALTA REMS [see Warnings and Precautions (5.2)].

1 INDICATIONS AND USAGE

1.1 Paroxysmal Nocturnal Hemoglobinuria

FABHALTA is indicated for the treatment of adults with paroxysmal nocturnal hemoglobinuria (PNH).

1.2 Immunoglobulin A Nephropathy

FABHALTA is indicated to reduce proteinuria in adults with primary immunoglobulin A nephropathy (IgAN) at risk of rapid disease progression, generally a urine protein-to-creatinine ratio (UPCR) ≥ 1.5 g/g.

This indication is approved under accelerated approval based on reduction of proteinuria. It has not been established whether FABHALTA slows kidney function decline in patients with IgAN. Continued approval for this indication may be contingent upon verification and description of clinical benefit in a confirmatory clinical trial.

1.3 Complement 3 Glomerulopathy

FABHALTA is indicated for the treatment of adults with complement 3 glomerulopathy (C3G), to reduce proteinuria.

2 DOSAGE AND ADMINISTRATION

2.1 Recommended Vaccination and Prophylaxis for Encapsulated Bacterial Infections

Vaccinate patients against encapsulated bacteria, including Streptococcus pneumoniae and Neisseria meningitidis (serogroups A, C, W, Y and B), according to current ACIP recommendations at least 2 weeks prior to initiation of FABHALTA [see Warnings and Precautions (5.1)].

If urgent FABHALTA therapy is indicated in a patient who is not up to date with vaccines for Streptococcus pneumoniae and Neisseria meningitidis according to ACIP recommendations, provide the patient with antibacterial drug prophylaxis and administer these vaccines as soon as possible [see Warnings and Precautions (5.1)].

Healthcare providers who prescribe FABHALTA must enroll in the FABHALTA REMS [see Warnings and Precautions (5.2)].

2.2 Recommended Dosage

The recommended dosage of FABHALTA is 200 mg orally twice daily without regard to food.

Swallow capsules whole. Do not open, break, or chew capsules.

If a dose or doses are missed, advise the patient to take one dose of FABHALTA as soon as possible (even if it is soon before the next scheduled dose) and then to resume the regular dosing schedule.

2.3 PNH Patients Switching From Anti-C5 (eculizumab, ravulizumab) to FABHALTA

To reduce the potential risk of hemolysis with abrupt discontinuation of other PNH therapies:

- For patients switching from eculizumab, initiate FABHALTA no later than 1 week after the last dose of eculizumab.
- For patients switching from ravulizumab, initiate FABHALTA no later than 6 weeks after the last dose of ravulizumab.

There is no available information regarding the timeframe for initiation of FABHALTA after other PNH therapies.

3 DOSAGE FORMS AND STRENGTHS

Capsules: 200 mg of iptacopan in pale yellow, opaque, hard gelatin capsules imprinted with “LNP200” on the body and “NVR” on the cap.

4 CONTRAINDICATIONS

FABHALTA is contraindicated:

- in patients with serious hypersensitivity to iptacopan or any of the excipients.
- for initiation in patients with unresolved serious infection caused by encapsulated bacteria, including Streptococcus pneumoniae, Neisseria meningitidis, or Haemophilus influenzae type b.

5 WARNINGS AND PRECAUTIONS

5.1 Serious Infections Caused by Encapsulated Bacteria

FABHALTA, a complement inhibitor, increases a patient’s susceptibility to serious, life-threatening, or fatal infections caused by encapsulated bacteria, including Streptococcus pneumoniae, Neisseria meningitidis (caused by any serogroup, including non-groupable strains), and Haemophilus influenzae type b. Life-threatening and fatal infections with encapsulated bacteria have occurred in both vaccinated and unvaccinated patients treated with complement inhibitors. The initiation of FABHALTA treatment is contraindicated in patients with unresolved serious infections caused by encapsulated bacteria.

Complete or update vaccination against encapsulated bacteria at least 2 weeks prior to administration of the first dose of FABHALTA, according to the current ACIP recommendations for patients receiving a complement inhibitor. Revaccinate patients in accordance with ACIP recommendations considering the duration of therapy with FABHALTA. Note that ACIP recommends an administration schedule in patients receiving complement inhibitors that differs from the administration schedule in the vaccine prescribing information. If urgent FABHALTA therapy is indicated in a patient who is not up to date with vaccines against encapsulated bacteria according to ACIP recommendations, provide the patient with antibacterial drug prophylaxis and administer these vaccines as soon as possible. Various durations and regimens of antibacterial drug prophylaxis have been considered, but the optimal durations and drug regimens for prophylaxis and their efficacy have not been studied in unvaccinated or vaccinated patients receiving complement inhibitors, including FABHALTA. The benefits and risks of treatment with FABHALTA, as well as the benefits and risks of antibacterial drug prophylaxis in unvaccinated or vaccinated patients, must be considered against the known risks for serious infections caused by encapsulated bacteria.

Vaccination does not eliminate the risk of serious encapsulated bacterial infections, despite development of antibodies following vaccination. Closely monitor patients for early signs and symptoms of serious infection and evaluate patients immediately if an infection is suspected. Inform patients of these signs and symptoms and instruct patients to seek immediate medical care if these signs and symptoms occur. Promptly treat known infections. Serious infection may become rapidly life-threatening or fatal if not recognized and treated early. Consider interruption of FABHALTA in patients who are undergoing treatment for serious infections, depending on the risks of interrupting treatment in the disease being treated.

FABHALTA is available only through a restricted program under a REMS [see Warnings and Precautions (5.2)].

5.2 FABHALTA REMS

FABHALTA is available only through a restricted program under a REMS called FABHALTA REMS, because of the risk of serious infections caused by encapsulated bacteria [see Warnings and Precautions (5.1)].

Notable requirements of the FABHALTA REMS include the following:

- Prescribers must enroll in the REMS.
- Prescribers must counsel patients about the risk of serious infections caused by encapsulated bacteria.
- Prescribers must provide patients with the REMS educational materials.
- Prescribers must assess patient vaccination status for vaccines against encapsulated bacteria and vaccinate if needed according to current ACIP recommendations two weeks prior to the first dose of FABHALTA.
- Prescribers must provide a prescription for antibacterial drug prophylaxis if treatment must be started urgently, and the patient is not up to date with vaccines against encapsulated bacteria according to current ACIP recommendations at least two weeks prior to the first dose of FABHALTA.
- Pharmacies that dispense FABHALTA must be certified in the FABHALTA REMS and must verify prescribers are certified.
- Patients must receive counseling from the prescriber about the need to receive vaccinations against encapsulated bacteria per ACIP recommendations, the need to take antibiotics as directed by the prescriber, and the early signs and symptoms of serious infections.
- Patients must be instructed to carry the Patient Safety Card with them at all times during treatment and for 2 weeks following the last dose of FABHALTA.

Further information is available by telephone: 1-833-99FABHA (1-833-993-2242) or online at www.FABHALTA-REMS.com.

5.3 Monitoring of PNH Manifestations After FABHALTA Discontinuation

In PNH patients, after discontinuing treatment with FABHALTA, closely monitor patients for at least 2 weeks after the last dose for signs and symptoms of hemolysis. These signs include elevated lactate dehydrogenase (LDH) levels along with a sudden decrease in hemoglobin or PNH clone size, fatigue, hemoglobinuria, abdominal pain, dyspnea, major adverse vascular events (such as thrombosis, stroke and myocardial infarction), dysphagia, or erectile dysfunction. If discontinuation of FABHALTA is necessary, consider alternative therapy.

If hemolysis occurs after discontinuation of FABHALTA, consider restarting treatment with FABHALTA, if appropriate, or initiating another treatment for PNH.

5.4 Hyperlipidemia

FABHALTA may increase total cholesterol, LDL-cholesterol, and serum triglycerides [see Adverse Reactions (6.1)].

Of the 54 FABHALTA-treated patients who had a normal total cholesterol level at baseline in APPLY-PNH, 43% developed Grade 1 hypercholesterolemia during the randomized treatment period. One FABHALTA-treated patient in APPLY-PNH experienced increased total cholesterol that worsened to Grade 2 from Grade 1 at baseline.

Of the 34 FABHALTA-treated patients who had a normal cholesterol level at baseline in APPOINT-PNH, 24% developed Grade 1 hypercholesterolemia during the core treatment period.

Of the 60 FABHALTA-treated patients who had LDL-cholesterol ≤ 130 mg/dL at baseline in APPLY-PNH, 17% developed LDL-cholesterol > 130-160 mg/dL, 8% developed LDL-cholesterol > 160-190 mg/dL, and 7% developed LDL-cholesterol > 190 mg/dL during the randomized treatment period. Of the 36 FABHALTA-treated patients who had LDL-cholesterol ≤ 130 mg/dL at baseline in APPOINT-PNH, 11% developed LDL-cholesterol > 130-160 mg/dL and 3% developed LDL-cholesterol > 160-190 mg/dL.

Of the 52 patients with normal triglyceride levels at baseline in APPLY-PNH, 23% developed Grade 1 elevated triglycerides during the randomized treatment period. Three FABHALTA-treated patients in APPLY-PNH experienced an increase in triglycerides from Grade 1 to Grade 2.

Of the 37 FABHALTA-treated patients who had a normal triglyceride level at baseline in APPOINT-PNH, 27% developed Grade 1 elevated triglycerides in the core treatment period.

Of the 102 FABHALTA-treated patients in APPLY-PNH and APPOINT-PNH, two patients required cholesterol-lowering medications.

Monitor serum lipid parameters periodically during treatment with FABHALTA and initiate cholesterol-lowering medication, if indicated.

6 ADVERSE REACTIONS

The following clinically significant adverse reactions are discussed in greater detail in other sections of the labeling:

- Serious Infections Caused by Encapsulated Bacteria [see Warnings and Precautions (5.1)].
- Hyperlipidemia [see Warnings and Precautions (5.4)].

6.1 Clinical Trials Experience

Because clinical trials are conducted under widely varying conditions, adverse reaction rates observed in the clinical trials of a drug cannot be directly compared to rates in the clinical trials of another drug and may not reflect the rates observed in practice.

Paroxysmal Nocturnal Hemoglobinuria (PNH)

The data described below reflects the exposure in adults with PNH who received FABHALTA (n = 62) or anti-C5 treatment (US-approved and non-US-approved eculizumab product or US-approved and non-US-approved ravulizumab product, n = 35) in APPLY-PNH [NCT04558918] and adults who received FABHALTA (n = 40) in APPOINT-PNH [NCT04820530] at the recommended dosing regimen for 24 weeks. In APPLY-PNH, serious adverse reactions were reported in 2 (3%) patients with PNH receiving FABHALTA. Serious adverse reactions included pyelonephritis, urinary tract infection and COVID-19. In APPOINT-PNH, serious adverse reactions were reported in 2 (5%) patients with PNH receiving FABHALTA. Serious adverse reactions included COVID-19 and bacterial pneumonia. The most common adverse reactions (≥ 10%) with FABHALTA were headache, nasopharyngitis, diarrhea, abdominal pain, bacterial infection, viral infection, nausea, and rash.

Table 1 describes the adverse reactions that occurred in > 5% of patients treated with FABHALTA in the APPLY-PNH or APPOINT-PNH studies.

Table 1: Adverse Reactions Reported in > 5% of Patients Treated with FABHALTA in APPLY-PNH or APPOINT-PNH Studies (24-Week Treatment Period)
Adverse reactions | APPLY-PNH |  | APPOINT-PNH
 | FABHALTA (N = 62) n (%) | Anti-C5 (Eculizumab or Ravulizumab) (N = 35) n (%) | FABHALTA (N = 40) n (%)
Headachea | 12 (19) | 1 (3) | 11 (28)
Nasopharyngitisb | 10 (16) | 6 (17) | 6 (15)
Diarrhea | 9 (15) | 2 (6) | 3 (8)
Abdominal paina | 9 (15) | 1 (3) | 3 (8)
Bacterial infectionc | 7 (11) | 4 (11) | 2 (5)
Nausea | 6 (10) | 1 (3) | 2 (5)
Viral infectiond | 6 (10) | 11 (31) | 7 (18)
Arthralgia | 5 (8) | 1 (3) | 0
Thrombocytopeniaa | 4 (6) | 0 | 0
Dizziness | 4 (6) | 0 | 1 (3)
Systemic hypertensiona | 4 (6) | 0 | 0
Lipid disordere | 4 (6) | 0 | 3 (8)
Rashf | 2 (3) | 0 | 4 (10)
aIncludes similar terms.
bNasopharyngitis contains: rhinitis allergic, upper respiratory tract infection, pharyngitis, rhinitis.
cBacterial infection contains: pyelonephritis, urinary tract infection, bronchitis bacterial, bronchitis haemophilus, cholecystitis, folliculitis, cellulitis, arthritis bacterial, sepsis, klebsiella infection, staphylococcal infection, Pseudomonas infection, hordeolum, pneumonia bacterial.
dViral infection contains: COVID-19, herpes zoster, oral herpes, nasal herpes, influenza A virus test positive, influenza.
eLipid disorder contains: dyslipidemia, blood cholesterol increased, low density lipoprotein increased, hypercholesterolemia, blood triglycerides increased, hyperlipidemia.
fRash contains: dermatitis allergic, acne, erythema multiforme, rash maculo-papular, rash erythematous.

Clinically relevant adverse reactions reported in less than or equal to 5% of patients includes urticaria in one patient (3%) in APPOINT-PNH.

Description of Select Adverse Reactions (graded per NCI CTCAE Version 4.03 unless noted otherwise)

Platelet Count Decreased

Of the 37 FABHALTA-treated patients who had normal platelet counts at baseline in APPLY-PNH, 43% experienced any Grade thrombocytopenia during the randomized treatment period. Three FABHALTA-treated patients in APPLY-PNH experienced decreased platelets that worsened to Grade ≥ 3 from baseline (one patient with normal platelets that worsened to Grade 4, one patient with baseline Grade 1 that worsened to Grade 4, and one patient with baseline Grade 3 that worsened to Grade 4).

Immunoglobulin A Nephropathy (IgAN)

The safety of FABHALTA was evaluated in APPLAUSE-IgAN, a randomized placebo-controlled, double-blind clinical study in adults with IgAN (eGFR ≥ 20 mL /min/1.73 m^2 at baseline).

The data below reflect FABHALTA exposure in 235 patients with IgAN (eGFR ≥ 20 mL/min/1.73 m^2 at baseline) with a median duration of 43 weeks (up to 104 weeks) in APPLAUSE-IgAN. Table 2 describes the adverse reactions that occurred in ≥ 3 % of patients treated with FABHALTA and were ≥ 2% higher in frequency than placebo. All of these adverse reactions were mild or moderate in severity.

Table 2: Adverse Reactions Reported in ≥ 3% of Adult Patients with IgAN (eGFR ≥ 20 mL /min/1.73 m^2) Treated with FABHALTA and ≥ 2% Higher in Frequency Than Placebo in APPLAUSE-IgAN
Adverse reaction | FABHALTA (N = 235) n (%) | Placebo (N = 235) n (%)
Upper respiratory tract infection | 20 (9) | 16 (7)
Lipid disorder^1 | 15 (6) | 10 (4)
Abdominal pain^1 | 15 (6) | 5 (2)
Nausea | 8 (3) | 2 (1)
Dizziness | 7 (3) | 2 (1)
^1Includes similar terms.

Complement 3 Glomerulopathy (C3G)

The safety of FABHALTA was evaluated in APPEAR-C3G, a randomized, placebo-controlled, double-blind trial in adult patients with native kidney C3G. No new adverse reactions were identified during the 6-month placebo-controlled period of APPEAR-C3G, in which 38 patients were treated with FABHALTA and 36 patients were treated with placebo. The most common adverse reactions that occurred in ≥ 10% of patients treated with FABHALTA and were ≥ 5% higher in frequency than placebo were nasopharyngitis (11% in FABHALTA, 3% placebo) and viral infections (29% in FABHALTA, 22% placebo), mainly respiratory infections. One patient (3%) on FABHALTA and none on placebo had a serious adverse reaction of pneumonia and bacteremia secondary to an encapsulated organism (S. pneumoniae).

7 DRUG INTERACTIONS

7.1 CYP2C8 Inducers

Concomitant use of CYP2C8 inducers (e.g., rifampin) may decrease iptacopan exposure, which may result in loss of or reduced efficacy of FABHALTA. Monitor the clinical response and discontinue use of the CYP2C8 inducer if loss of efficacy of FABHALTA is evident.

7.2 Strong CYP2C8 Inhibitors

Concomitant use of strong CYP2C8 inhibitors (e.g., gemfibrozil) may increase iptacopan exposure, which may result in an increased risk for adverse reactions with FABHALTA. Coadministration with a strong CYP2C8 inhibitor is not recommended.

8 USE IN SPECIFIC POPULATIONS

8.1 Pregnancy

Risk Summary

Available data from clinical trials with FABHALTA use in pregnant women are insufficient to identify a drug-associated risk of major birth defects, miscarriage, or other adverse maternal or fetal outcomes. There are risks to the mother and fetus associated with untreated PNH, IgAN, or C3G in pregnancy (see Clinical Considerations). The use of FABHALTA in pregnant women or women planning to become pregnant may be considered following an assessment of the risks and benefits.

In animal reproduction studies, oral administration of iptacopan to pregnant rats and rabbits during organogenesis at exposures 4- to 6-times the human exposure (based on AUC) at the maximum recommended human dose (MRHD) of 200 mg twice daily did not induce embryo or fetal toxicity (see Data).

The estimated background risk of major birth defects and miscarriage for the indicated populations is unknown. All pregnancies have a background risk of major birth defects, loss, or other adverse outcomes. In the U.S. general population, the estimated background risk of major birth defects and miscarriages in clinically recognized pregnancies is 2% to 4% and 15% to 20%, respectively.

Clinical Considerations

Disease-Associated Maternal and/or Embryo/Fetal Risk

PNH in pregnancy is associated with adverse maternal outcomes, including worsening cytopenias, thrombosis, infections, bleeding, miscarriages, increased maternal mortality, and adverse fetal outcomes, including fetal death and premature delivery.

IgAN in pregnancy is associated with adverse maternal outcomes, including increased rates of cesarean section, pregnancy-induced hypertension, pre-eclampsia and preterm delivery, and adverse fetal/neonatal outcomes, including stillbirth and low birth weight.

C3G in pregnancy may be associated with adverse maternal outcomes, in particular preeclampsia and miscarriage, as well as adverse fetal outcomes including prematurity and low birth weight.

Data

Animal Data

In an embryo-fetal development study in rats, oral administration of iptacopan during organogenesis did not cause embryo-fetal toxicity when given up to the highest dose of 1,000 mg/kg/day, which corresponds to 4-times the MRHD based on AUC.

In an embryo-fetal development study in rabbits, oral administration of iptacopan during organogenesis did not cause embryo-fetal toxicity when given up to the highest dose of 450 mg/kg/day, which corresponds to 6-times the MRHD based on AUC.

In a pre- and postnatal development study in rats, oral administration of iptacopan during gestation, parturition, and lactation did not cause adverse effects in offspring when given up to the highest dose of 1,000 mg/kg/day, which corresponds to 4-times the MRHD based on AUC.

8.2 Lactation

Risk Summary

There are no data on the presence of iptacopan or its metabolites in either human or animal milk, the effects on the breastfed child or on milk production. Since many medicinal products are secreted into human milk, and because of the potential for serious adverse reactions in a breastfed child, breastfeeding should be discontinued during treatment and for 5 days after the final dose.

8.4 Pediatric Use

Safety and effectiveness in pediatric patients with PNH, IgAN, or C3G have not been established.

8.5 Geriatric Use

There were 29 PNH patients 65 years of age and older in APPLY-PNH and APPOINT-PNH [see Clinical Studies (14)]. Of the total number of FABHALTA-treated patients during the 24-week treatment period in these studies, 21 (20.6%) were 65 years of age and older, while 7 (6.9%) were 75 years of age and older. There were 8 IgAN patients 65 years of age and older in APPLAUSE-IgAN [see Clinical Studies (14)]. Of the total number of FABHALTA-treated patients, 3 (2.4%) were 65 years of age and older. Clinical studies of FABHALTA did not include sufficient numbers of patients 65 years of age and older to determine whether they respond differently from younger patients.

8.7 Hepatic Impairment

The use of FABHALTA is not recommended in patients with severe hepatic impairment (Child-Pugh class C). No dose adjustment is required for patients with mild (Child-Pugh class A) or moderate (Child-Pugh class B) hepatic impairment [see Clinical Pharmacology (12.3)].

11 DESCRIPTION

FABHALTA contains iptacopan, a complement Factor B inhibitor. The molecular weight of iptacopan hydrochloride monohydrate is approximately 477 g/mol. The chemical name is (2S,4S)-2-(4-Carboxyphenyl)-4-ethoxy-1-[(5-methoxy-7-methyl-1H-indol-4-yl)methyl]piperidin-1-ium chloride―water (1/1). The molecular formula is C25H30N2O4·HCl H2O. The structure is shown below.

Iptacopan hydrochloride monohydrate is a white or almost white to pale purplish-pink powder.

FABHALTA is supplied as hard gelatin capsules for oral administration. The capsules are packaged in high-density polyethylene (HDPE) bottles with induction seals and child resistant caps. Each FABHALTA capsule contains 200 mg iptacopan (provided as 225.8 mg iptacopan hydrochloride monohydrate) and the capsule shell contains the following inactive ingredients: gelatin, red ferric oxide, titanium dioxide, yellow ferric oxide. The black printing ink contains ferrosoferric oxide, potassium hydroxide, propylene glycol, shellac, and strong ammonia solution.

12 CLINICAL PHARMACOLOGY

12.1 Mechanism of Action

Iptacopan binds to Factor B of the alternative complement pathway and regulates the cleavage of C3, generation of downstream effectors, and the amplification of the terminal pathway.

In PNH, intravascular hemolysis (IVH) is mediated by the downstream membrane attack complex (MAC), while extravascular hemolysis (EVH) is facilitated by C3b opsonization. Iptacopan acts proximally in the alternative pathway of the complement cascade to control both C3b-mediated EVH and terminal complement-mediated IVH.

In IgAN, the deposition of galactose deficient IgA1 (Gd-IgA1) containing immune complexes in the kidney locally activates the alternative complement pathway which is thought to contribute to the pathogenesis of IgAN. By binding to Factor B, iptacopan inhibits the alternative pathway.

In C3G, overactivation of the alternative complement pathway leads to C3 cleavage within the glomeruli resulting in C3 deposition and inflammation, which are thought to contribute to the pathogenesis of C3G. By binding to Factor B, iptacopan inhibits the alternative pathway.

12.2 Pharmacodynamics

Inhibition of the alternative complement pathway biomarkers, the in vitro alternative pathway assay and plasma Bb (fragment Bb of Factor B), started approximately 2 hours after a single iptacopan dose in healthy volunteers.

In PNH patients receiving concomitant anti-C5 treatment and FABHALTA 200 mg twice daily, the in vitro alternative pathway assay and plasma Bb decreased from baseline by 54.1% and 56.1%, respectively, on the first observation on Day 8. In treatment naïve PNH patients, these same biomarkers decreased from baseline by 78.4% and 58.9%, respectively, on the first observation after 4 weeks of treatment with FABHALTA 200 mg twice daily.

In PNH patients on concomitant anti-C5 treatment and FABHALTA 200 mg twice daily, the mean PNH red blood cell (RBC) clone size was 54.8% at baseline and increased to 89.2% after 13 weeks; the proportion of PNH Type II + III RBCs with C3 deposition was 12.4% at baseline and decreased to 0.2% after 13 weeks. In treatment naïve PNH patients, the mean PNH RBC clone size was 49.1% at baseline and increased to 91.1% after 12 weeks; there were negligible PNH Type II + III RBCs with C3 deposition in this population due to the predominance of IVH.

Iptacopan reduces serum LDH levels. In PNH patients previously treated with eculizumab, all patients treated with FABHALTA 200 mg twice daily achieved a reduction of LDH levels to < 1.5 times the upper limit of normal (ULN) at 13 weeks. In treatment naïve PNH patients, FABHALTA 200 mg twice daily reduced LDH by > 60% compared to baseline after 12 weeks and maintained the effect through the end of the study at 2 years.

In IgAN patients receiving 200 mg twice daily, the in vitro alternative pathway assay, plasma Bb, plasma soluble C5b-9 (also known as MAC), and urine soluble C5b-9 decreased from baseline by 85.2%, 17.5%, 19.5% and 96.5%, respectively, on the first observation at Month 9.

In C3G patients receiving 200 mg twice daily, the geometric mean serum C3 at baseline was 23 mg/dL and increased to 80 mg/dL at Day 14 of FABHALTA treatment. Over this same period, the placebo group geometric mean serum C3 level decreased from 25 mg/dL to 24 mg/dL. At 6 months the mean glomerular C3 deposition score (0-12) decreased by 0.8 (95% CI: -0.3, 1.8) from a baseline of 9.2 with FABHALTA and increased by 1.1 (95% CI: 0.1, 2.1) from a baseline of 9.6 with placebo. Plasma soluble C5b-9 (also known as MAC) and urine soluble C5b-9 decreased from baseline by 67% and 88%, respectively, at Day 180 of treatment with FABHALTA 200 mg twice daily compared to a 3% decrease in plasma soluble C5b-9 and a 36% decrease in urine soluble C5b-9 in the placebo group.

Cardiac Electrophysiology

In a QTc clinical study in healthy volunteers, single supra-therapeutic iptacopan doses up to 1,200 mg (which provided greater than 4-fold peak concentration of the MRHD) showed no effect on cardiac repolarization or QT interval.

12.3 Pharmacokinetics

Absorption

Following oral administration, iptacopan reached peak plasma concentrations approximately 2 hours post dose. At the recommended dosing regimen of 200 mg twice daily, steady state is achieved in approximately 5 days with minor accumulation (1.4-fold).

Effect of Food

Based on a food-effect study in healthy volunteers, a high-fat meal did not affect the exposure of iptacopan to a clinically meaningful degree.

Distribution

Iptacopan showed concentration-dependent plasma protein binding due to binding to the target Factor B in the systemic circulation. Iptacopan was 75% to 93% protein bound in vitro at the relevant clinical plasma concentrations. After administration of iptacopan 200 mg twice daily, the apparent volume of distribution at steady state was approximately 288 L.

Elimination

The terminal half-life (t1/2) of iptacopan at steady state is approximately 25 hours after administration of FABHALTA 200 mg twice daily. The apparent clearance of iptacopan at steady state is 8 L/h after administration of FABHALTA 200 mg twice daily.

Metabolism

Metabolism is a predominant elimination pathway for iptacopan with approximately 50% of the dose attributed to oxidative pathways. Metabolism of iptacopan includes N-dealkylation, O-deethylation, oxidation, and dehydrogenation, mostly driven by CYP2C8 (98%) with a small contribution from CYP2D6 (2%). Iptacopan undergoes Phase 2 metabolism through glucuronidation by UGT1A1, UGT1A3, and UGT1A8. In plasma, iptacopan was the major component, accounting for 83% of the drug-related species. Two acyl glucuronides were the only metabolites detected in plasma and were minor, accounting for 8% and 5% of the drug-related species. Iptacopan metabolites are not pharmacologically active.

Excretion

In a human study, following a single 100 mg oral dose of [^14C]-iptacopan, mean total excretion of radioactivity (iptacopan and metabolites) was 72% in the feces and 25% in the urine, for a total mean excretion of > 96% of the dose. Specifically, 18% of the dose was excreted as parent iptacopan in the urine, and 17% of the dose was excreted as parent iptacopan in feces.

Linearity/Non-linearity

At doses between 25 mg and 200 mg twice daily, iptacopan was overall less than dose proportional. However, oral doses of 100 mg and 200 mg were approximately dose proportional.

Specific Populations

A population pharmacokinetic (PK) analysis was conducted on iptacopan data from 234 patients. Age, body weight, race, and gender did not have a clinically significant effect on iptacopan PK.

Patients with Renal Impairment

There were no clinically significant differences in the exposure of FABHALTA between patients with an eGFR in the range of 25 to < 90 mL/min compared to those with normal eGFR. No data are currently available in patients on dialysis.

Patients with Hepatic Impairment

In a study in subjects with normal hepatic function and patients with mild (Child-Pugh class A), moderate (Child-Pugh class B), or severe hepatic impairment (Child-Pugh class C), there was a negligible effect of hepatic impairment on the total (bound+unbound) exposure of iptacopan. However, unbound iptacopan AUCinf increased by 48%, 58% and 271% in patients with mild, moderate, and severe hepatic impairment, respectively, compared to subjects with normal hepatic function.

Drug Interaction Studies

Based on a clinical drug interaction study in healthy volunteers, iptacopan exposure did not change to a clinically relevant degree when coadministered with clopidogrel (a moderate CYP2C8 inhibitor) or cyclosporine (a P-gp, BCRP, and OATP 1B1/1B3 inhibitor). The exposure of digoxin (a P-gp substrate) and rosuvastatin (an OATP substrate) did not change to a clinically relevant degree when coadministered with iptacopan.

13 NONCLINICAL TOXICOLOGY

13.1 Carcinogenesis, Mutagenesis, Impairment of Fertility

Iptacopan was not genotoxic or mutagenic in a battery of in vitro and in vivo assays.

Carcinogenicity studies conducted with oral administration of iptacopan in RasH2 transgenic mice with doses up to 1,000 mg/kg/day for 6 months and in rats with doses up to 750 mg/kg/day for 2 years did not identify any carcinogenic potential. The highest exposure to iptacopan in rats corresponds to approximately 9-times the MRHD based on AUC.

In a fertility study in male rats, iptacopan did not adversely impact fertility up to the highest tested dose of 750 mg/kg/day, which corresponds to 4-times the MRHD based on AUC. Reversible effects on the male reproductive system (testicular tubular degeneration and cellular debris in epididymis) were observed in repeat-dose toxicity studies with oral administration in dogs at doses ≥ 2-times the MRHD based on AUC, with no clear effects on sperm numbers, morphology, or motility. In a fertility and early embryonic developmental study in female rats, oral administration of iptacopan caused increased pre- and post-implantation losses when given at the highest dose of 1,000 mg/kg/day orally, which corresponds to approximately 11-times the MRHD based on AUC.

14 CLINICAL STUDIES

14.1 Paroxysmal Nocturnal Hemoglobinuria (PNH)

APPLY-PNH: Anti-C5 Treatment Experienced Patients With PNH

The efficacy of FABHALTA administered orally in adults with PNH was evaluated in a multi-center, open-label, 24-week, active comparator-controlled trial (APPLY-PNH; NCT04558918).

The study enrolled adults with PNH and residual anemia (hemoglobin < 10 g/dL) despite previous treatment with a stable regimen of anti-C5 treatment (either eculizumab or ravulizumab) for at least 6 months prior to randomization.

Ninety-seven patients were randomized in an 8:5 ratio to switch to FABHALTA 200 mg orally twice daily (n = 62) or to continue anti-C5 treatment (US-approved and non-US-approved eculizumab product n = 23 or US-approved and non-US-approved ravulizumab product n = 12) throughout the duration of the 24-week randomized controlled period. Randomization was stratified based on prior anti-C5 treatment and transfusion history within the last 6 months. Following completion of the 24-week randomized controlled period, all patients were eligible to enroll in a 24-week treatment extension period and receive FABHALTA monotherapy. Subsequently, patients were eligible to enter a separate long-term extension study.

Patients were required to be vaccinated against Neisseria meningitidis and recommended to be vaccinated against Streptococcus pneumoniae and Haemophilus influenzae type b. If the patient had not been previously vaccinated or if a booster was required, vaccination was administered at least 2 weeks prior to the first dose of study medication. If FABHALTA treatment was initiated earlier than 2 weeks after vaccination, antibacterial drug prophylaxis was administered.

Demographics and baseline disease characteristics were generally well balanced between treatment groups (see Table 3). The mean time on prior anti-C5 treatment was 3.8 and 4.2 years for the FABHALTA and anti-C5 groups, respectively. The baseline mean PNH RBC clone size (Type II + III) was 64.6% for the FABHALTA group and 57.4% for the anti-C5 group.

Table 3: Patient Baseline Demographics and Characteristics in APPLY-PNH
Parameters | Statistics | FABHALTA (n = 62) | Anti-C5 (Eculizumab or Ravulizumab) (n = 35)
Age (years) | Mean (SD) min, max | 51.7 (16.9) 22, 84 | 49.8 (16.7) 20, 82
Sex Female | n (%) | 43 (69.4) | 24 (68.6)
Race White Asian Black or African American | n (%) n (%) n (%) | 48 (77.4) 12 (19.4) 2 (3.2) | 26 (74.3) 7 (20.0) 2 (5.7)
Ethnicity Not Hispanic or Latino Hispanic or Latino Not reported/unknown | n (%) n (%) n (%) | 51 (82.3) 8 (12.9) 3 (4.8) | 27 (77.1) 2 (5.7) 6 (17.1)
Hemoglobin level (g/dL) | Mean (SD) | 8.9 (0.7) | 8.9 (0.9)
LDH level (U/L) | Mean (SD) | 269 (70) | 273 (85)
Absolute reticulocyte count (ARC) (10^9/L) | Mean (SD) | 193 (84) | 191 (81)
At least one transfusion in 6 months prior to randomization | n (%) | 35 (56.5) | 21 (60.0)
History of MAVEs | n (%) | 12 (19.4) | 10 (28.6)
Disease duration (years) | Mean (SD) | 11.9 (9.8) | 13.5 (10.9)
Abbreviations: LDH, lactate dehydrogenase; MAVEs, major adverse vascular events (includes thrombosis, stroke and myocardial infarction); SD, standard deviation.

Efficacy was established based on demonstration of superiority of switching to FABHALTA compared to continuing on anti-C5 therapy in achieving hematological response after 24 weeks of treatment, without a need for transfusion, by assessing the proportion of patients demonstrating: 1) sustained increase of ≥ 2 g/dL in hemoglobin levels from baseline (hemoglobin improvement) and 2) sustained hemoglobin levels ≥ 12 g/dL. Additional efficacy endpoints included transfusion avoidance, change from baseline in hemoglobin levels and change from baseline in absolute reticulocyte counts.

The efficacy results from the APPLY-PNH trial are provided in Table 4.

Table 4: Efficacy Results for the 24-week Randomized Treatment Period for APPLY-PNH
Endpoints | FABHALTA (N = 62) | Anti-C5 (Eculizumab or Ravulizumab) (N = 35) | Difference (95% CI) p-value
Primary endpoints
Patients with sustained increase of hemoglobin levels ≥ 2 g/dLa from baseline in the absence of transfusions Response rate (%) (95% CI) | 51/62 82.3 (70.5, 90.8) | 0/35 0 (0, 10.0) | 81.5b (71.6, 91.4) < 0.0001
Patients with sustained hemoglobin level ≥ 12 g/dLa in the absence of transfusions Response rate (%) (95% CI) | 42/62 67.7 (54.7, 79.1) | 0/35 0 (0, 10.0) | 66.6b (54.6, 78.6) < 0.0001
Secondary endpoints
Patients avoiding transfusionc,d Transfusion avoidance rate (%) (95% CI) | 59/62 95.2 (86.5, 99.0) | 16/35 45.7 (28.8, 63.4) | 49.5b (32.5, 66.6) < 0.0001
Hemoglobin change from baseline (g/dL) (adjusted meane,f) (95% CI) | 3.6 (3.3, 3.9) | -0.1 (-0.5, 0.3) | 3.7 (3.2, 4.1) < 0.0001
Absolute reticulocyte count change from baseline (10^9/L) (adjusted meane) (95% CI) | -116 (-127, -105) | 0 (-13, 14) | -116 (-132, -100) < 0.0001
Abbreviations: RR, rate ratio.
aAssessed between Day 126 and 168.
bAdjusted difference in proportion.
cAssessed between Day 14 and 168.
dTransfusion avoidance is defined as absence of administration of packed-red blood cell transfusions between Day 14 and 168.
eAdjusted mean assessed between Day 126 and 168.
fExcludes values within 30 days post-transfusion.

APPOINT-PNH: Complement Inhibitor Naïve Patients with PNH

Study APPOINT-PNH (NCT04820530) is a single arm study in adults with PNH who were not previously treated with a complement inhibitor. This study enrolled a total of 40 adults with PNH (RBC clone size ≥ 10%), hemoglobin < 10 g/dL, and LDH > 1.5 times upper limit of normal (ULN). All 40 patients received FABHALTA 200 mg orally twice daily during the 24-week open-label core treatment period. Subsequently, patients were eligible to enroll in a 24-week treatment extension period and continue to receive FABHALTA, followed by a separate long-term extension study.

The mean age of the patients was 42.1 years and 42.5% were female. The mean disease duration was 4.7 years. The baseline mean PNH RBC clone size (Type II + III) was 42.7%, mean baseline hemoglobin was 8.2 g/dL, and approximately 70% of patients required a transfusion in the 6 months prior to treatment. The baseline mean LDH level was 1,699 U/L and the mean absolute reticulocyte count was 154 X 10^9/L. About 13% of patients had a history of MAVEs. No patients discontinued from the core treatment period of the study.

In total, 77.5% (95% CI: 61.5%, 89.2%) of patients (31/40) achieved a sustained increase (between Day 126 and Day 168) in hemoglobin levels from baseline of ≥ 2 g/dL in the absence of RBC transfusions, based on central laboratory hemoglobin values. In a sensitivity analysis, 87.5% (95% CI: 73.2%, 95.8%) of patients (35/40) achieved a sustained increase (between Day 126 and Day 168) in hemoglobin levels from baseline of ≥ 2 g/dL in the absence of RBC transfusions, including local laboratory hemoglobin values when central laboratory hemoglobin values were not available.

14.2 Immunoglobulin A Nephropathy (IgAN)

The effect of FABHALTA was evaluated in a multicenter, randomized, placebo-controlled, double-blind study (APPLAUSE-IgAN, NCT04578834) in adults with biopsy-proven IgAN, eGFR ≥ 20 mL/min/1.73 m^2, and urine protein-to-creatinine ratio (UPCR) ≥ 1 g/g on a stable dose of maximally-tolerated renin-angiotensin system (RAS) inhibitor therapy with or without a stable dose of an SGLT2 inhibitor. Patients with other glomerulopathies or those who had been recently treated with systemic immunosuppressants were excluded. Patients were included in either the Main Study Population (eGFR ≥ 30 mL/min/1.73 m^2) or the Severe Renal Impairment population (eGFR ≥ 20 and < 30 mL/min/1.73 m^2). Within each group, patients were randomized (1:1) to either FABHALTA 200 mg or placebo twice daily. Rescue immunosuppressive treatment could be initiated per investigator discretion during the trial.

Patients were required to be vaccinated against Neisseria meningitidis and Streptococcus pneumoniae and were recommended to be vaccinated against Haemophilus influenzae type b. If the patient had not been previously vaccinated or if a booster was required, vaccination was administered at least 2 weeks prior to first dosing. If FABHALTA treatment was initiated earlier than 2 weeks after vaccination, antibacterial drug prophylaxis was administered.

The efficacy analysis was based on the first 250 patients with an eGFR ≥ 30 mL/min/1.73 m^2 (Main Study Population), who had completed or discontinued the study prior to the Month 9 visit. At baseline, the mean age of these patients was 39 years (range 18 to 74 years); 52% were male, 44% White, 54% Asian, and < 1% Black or African American; the mean eGFR was 64 mL/min/1.73 m^2; the geometric mean UPCR (sampled from a 24-hr urine collection) was 2.0 g/g, and 12% had a UPCR ≥ 3.5 g/g. At baseline, 99% of patients were treated with an ACEi or ARB and 13% were on an SGLT2i. Approximately 59% had a history of hypertension, 6% had a history of type 2 diabetes, and 75% had hematuria based on urine dipstick.

The primary endpoint was the percent reduction in UPCR (sampled from a 24-hr urine collection) at Month 9 relative to baseline (see Table 5). The mean percent change from baseline in UPCR over time is shown in Figure 1.

Table 5: Percent Reduction in UPCR at Month 9 in APPLAUSE-IgAN
 | FABHALTA (N = 125) | Placebo (N = 125)
Geometric mean of UPCR, g/g Baseline Month 9 | 1.9 (n = 125) 1.0 (n = 119) | 2.0 (n = 125) 1.7 (n = 110)
% reduction in UPCR at Month 9 relative to baseline (95% CI)a | 44% (36%, 51%) | 9% (-5%, 21%)
FABHALTA versus placebo: % reduction in UPCR at Month 9 relative to baseline (95% CI)a | 38% (26%, 49%)
p-valueb | < 0.0001
aPercent reduction in UPCR was obtained from the adjusted geometric mean ratios where the log transformed ratio to baseline in UPCR (sampled from 24hr urine collection) was analyzed using an MMRM; Values after taking rescue immunosuppressive treatment for IgAN were imputed to reflect disease worsening. Rescue immunosuppressive treatment for IgAN was initiated in 0 and 7 (5.6%) patients in the FABHALTA and placebo group up to Month 9, respectively.
bOne-sided p-value statistically significant at the 0.005 level.
Abbreviations: CI, confidence interval; IgAN, immunoglobulin A nephropathy; MMRM, mixed model of repeated measures; N, number of subjects in each group; n, number of subjects with available data at the time of analysis; UPCR, urine protein-to-creatinine ratio

Figure 1: Geometric Mean Percent Change from Baseline in UPCR by Visit in APPLAUSE-IgAN

Adjusted % change relative to baseline in UPCR were obtained by analyzing the log transformed ratio to baseline in UPCR using an MMRM as described in Table 5. N represents the number of subjects with values non-missing/not imputed as per the intercurrent event handling strategy by visit and treatment group.

Abbreviations: CI, confidence interval; FAB, FABHALTA; MMRM, mixed model repeated measures; N, number of subjects in each group; PBO, placebo; UPCR, urine protein-to-creatinine ratio.

The treatment effect on UPCR at Month 9 was consistent across all subgroups including age, sex, race, baseline disease characteristics (such as baseline eGFR and proteinuria levels), and the use of SGLT2i.

14.3 Complement 3 Glomerulopathy (C3G)

The efficacy of FABHALTA in reducing proteinuria in adult patients with native kidney C3G was demonstrated in the APPEAR-C3G trial. Safety and effectiveness of FABHALTA in patients with recurrent C3G following kidney transplant have not been established.

APPEAR-C3G was a randomized, double-blind, placebo-controlled study in 74 adult patients with biopsy confirmed native kidney C3G who had a urine protein-to-creatinine ratio (UPCR) ≥ 1 g/g and eGFR ≥ 30 mL/min/1.73 m^2 (NCT04817618). Patients were randomized (1:1) to receive either FABHALTA 200 mg orally twice daily (N = 38) or placebo (N = 36) for 6 months, followed by a 6-month open-label treatment period in which all patients received FABHALTA 200 mg orally twice daily.

Patients were required to be on a maximally tolerated renin-angiotensin system (RAS) inhibitor and could be on a corticosteroid and/or mycophenolate mofetil/sodium (MMF/MPS) at baseline. All background therapies (i.e., RAS inhibitors, corticosteroids and MMF/MPS) were required to be at stable doses for 90 days prior to randomization and throughout the study. Randomization was stratified according to whether patients were receiving concomitant immunosuppressive therapy.

Patients were required to be vaccinated against Neisseria meningitidis and Streptococcus pneumoniae and were recommended to be vaccinated against Haemophilus influenzae type b. If the patient had not been previously vaccinated or if a booster was required, vaccination was administered at least 2 weeks prior to first dosing. If FABHALTA treatment was initiated earlier than 2 weeks after vaccination, antibacterial drug prophylaxis was administered.

At baseline, the mean age of patients was 28 years (range 18 to 60 years), 64% were male, 69% were White, 24% were Asian, and 9% were Hispanic or Latino. The mean baseline eGFR (mL/min/1.73 m^2) was 89 and 99 in the FABHALTA and placebo groups, respectively, and the geometric mean 24-hour UPCR (g/g) at baseline was 3.3 and 2.6 in the FABHALTA and placebo groups, respectively.

Twenty four percent of patients in the FABHALTA group and 3% in the placebo group had dense deposit disease. Baseline use of corticosteroids and/or MMF/MPS, and RAS inhibitor was balanced among the FABHALTA and placebo groups. Overall, 45% of patients were on corticosteroids and/or MMF/MPS, and 99% of patients were on a RAS inhibitor at baseline.

The primary efficacy endpoint was the log-transformed ratio to baseline in UPCR (sampled from a 24-hour urine collection) at 6 months. At 6 months, the geometric mean UPCR ratio relative to baseline was 0.70 (95% CI: 0.57, 0.85) and 1.08 (95% CI: 0.88, 1.31) in the FABHALTA and placebo groups, respectively, resulting in a 35% reduction in 24-hour UPCR from baseline in the FABHALTA group compared to placebo (p = 0.0028).

Following the initial 6-month treatment period, all patients were treated with FABHALTA for an additional 6 months. In patients initially randomized to FABHALTA, the reduction in 24-hour UPCR seen at 6 months was maintained at Month 12. In patients who switched from placebo to FABHALTA, the magnitude of the reduction in 24-hour UPCR from Month 6 to 12 was similar to the reduction seen in patients initially randomized to FABHALTA. The geometric mean percent change from baseline in UPCR (measured as first morning void [FMV]) over time is shown in Figure 2.

Compared to patients treated with placebo, patients treated with FABHALTA had a 7-fold higher odds (p = 0.0166) of achieving a composite renal endpoint defined as a ≥ 50% reduction in 24-hour UPCR compared to baseline and stable or improved eGFR compared to baseline [≤ 15% reduction in eGFR] at 6 months. Although a greater proportion of patients in the FABHALTA arm (30%) as compared to placebo (6%) achieved a ≥ 50% reduction in 24-hour UPCR compared to baseline, there was no difference between arms in the proportion of patients with stable or improved eGFR compared to baseline at 6 months (90% in FABHALTA vs 89% in placebo).

Figure 2: Geometric Mean Percent Change from Baseline in UPCR FMV (g/g) up to Month 12 (APPEAR-C3G)

The treatment effect of FABHALTA on UPCR at Month 6 was generally consistent across subgroups including age, sex, race, baseline disease characteristics (such as baseline proteinuria and eGFR levels) and use of immunosuppressive therapies.

16 HOW SUPPLIED/STORAGE AND HANDLING

200 mg capsules: pale yellow opaque hard capsules, imprinted with “LNP200” on one half and “NVR” on the other half, packaged in a high-density polyethylene (HDPE) bottle with induction seal and child-resistant cap. Each bottle contains 60 capsules (NDC 0078-1189-20).

Store at 20°C to 25°C (68°F to 77°F); excursions permitted between 15°C and 30°C (59°F and 86°F) [see USP Controlled Room Temperature].

17 PATIENT COUNSELING INFORMATION

Advise the patient to read the FDA-approved patient labeling (Medication Guide).

Serious Infections Caused by Encapsulated Bacteria

Advise patients of the risk of serious infection. Inform patients of the need to complete or update their vaccinations against encapsulated bacteria at least 2 weeks prior to receiving the first dose of FABHALTA or to receive antibacterial drug prophylaxis if FABHALTA treatment must be initiated immediately and they have not been previously vaccinated. Inform patients of the requirement to be revaccinated according to current ACIP recommendations for encapsulated bacteria while on FABHALTA therapy [see Warnings and Precautions (5.1)].

Inform patients that vaccination may not prevent serious infection and to seek immediate medical attention if the following signs or symptoms occur [see Warnings and Precautions (5.1)]:

- fever with or without shivers or chills
- fever and a rash
- fever with chest pain and cough
- fever with breathlessness/fast breathing
- fever with high heart rate
- headache with nausea or vomiting
- headache and a fever
- headache with a stiff neck or stiff back
- confusion
- body aches with flu-like symptoms
- clammy skin
- eyes sensitive to light

Inform patients that they will be given a Patient Safety Card for FABHALTA that they should carry with them at all times during and for 2 weeks following treatment with FABHALTA. This card describes symptoms which, if experienced, should prompt the patient to seek immediate medical evaluation.

FABHALTA REMS

FABHALTA is available only through a restricted program called FABHALTA REMS [see Warnings and Precautions (5.2)].

Inform the patient of the following notable requirements:

- Patients must receive counseling about the risk of serious infections caused by encapsulated bacteria.
- Patients must receive written educational materials about this risk.
- Patients must be instructed to carry the Patient Safety Card with them at all times during and for 2 weeks following treatment with FABHALTA.
- Patients must be instructed to complete or update vaccines against encapsulated bacteria per ACIP recommendations as directed by the prescriber prior to treatment with FABHALTA.
- Patients must receive antibiotics as directed by the prescriber if they are not up to date on vaccinations against encapsulated bacteria and have to start FABHALTA right away.

Importance of Adherence to Dosing Schedule

Inform patients with PNH of the importance of taking FABHALTA as prescribed in order to minimize the risk of hemolysis.

Discontinuation

Inform patients with PNH that they may develop serious hemolysis due to PNH if FABHALTA is discontinued and that they should be monitored by their healthcare providers for at least 2 weeks following discontinuation of FABHALTA.

Inform patients who discontinue FABHALTA to keep the Patient Safety Card with them for 2 weeks after the last dose of FABHALTA. The increased risk of serious infection may continue for a few weeks after the last dose of FABHALTA.

Hyperlipidemia

Inform patients that FABHALTA may increase their cholesterol and triglycerides and that monitoring of these parameters will be needed periodically during treatment.

Distributed by:
Novartis Pharmaceuticals Corporation
East Hanover, New Jersey 07936
For more information, visit www.FABHALTA.com or call 1-888-669-6682.

© Novartis

T2025-15

MEDICATION GUIDE
FABHALTA® (fab hal tah)
(iptacopan)
capsules, for oral use

What is the most important information I should know about FABHALTA?
FABHALTA is a medicine that affects part of your immune system. FABHALTA may lower the ability of your immune system to fight infections.

- FABHALTA increases your chance of getting serious infections caused by encapsulated bacteria, including Streptococcus pneumoniae, Neisseria meningitidis, and Haemophilus influenzae type b. These serious infections may quickly become life-threatening or fatal if not recognized and treated early.
  - You must complete or update your vaccinations against Streptococcus pneumoniae and Neisseria meningitidis at least 2 weeks before your first dose of FABHALTA.
  - If you have not completed your vaccinations and FABHALTA must be started right away, you should receive the required vaccinations as soon as possible.
  - If you have not been vaccinated and FABHALTA must be started right away, you should also receive antibiotics to take for as long as your healthcare provider tells you.
  - If you have been vaccinated against these bacteria in the past, you might need additional vaccinations before starting FABHALTA. Your healthcare provider will decide if you need additional vaccinations.
  - Vaccines do not prevent all infections caused by encapsulated bacteria. Call your healthcare provider or get emergency medical care right away if you have any of these signs and symptoms of a serious infection:

▪ fever with or without shivers or chills
▪ fever with chest pain and cough
▪ fever with high heart rate
▪ headache and fever
▪ confusion
▪ clammy skin

▪ fever and a rash
▪ fever with breathlessness or fast breathing
▪ headache with nausea or vomiting
▪ headache with stiff neck or stiff back
▪ body aches with flu-like symptoms
▪ eyes sensitive to light

Your healthcare provider will give you a Patient Safety Card about the risk of serious infections. Carry it with you at all times during treatment and for 2 weeks after your last dose of FABHALTA. Your risk of serious infections may continue for a few weeks after your last dose of FABHALTA. It is important to show this card to any healthcare provider who treats you. This will help them diagnose and treat you quickly.
FABHALTA is only available through a program called the FABHALTA Risk Evaluation and Mitigation Strategy (REMS). Before you can take FABHALTA, your healthcare provider must:

- enroll in the FABHALTA REMS program
- counsel you about the risk of serious infections caused by certain bacteria
- give you information about the symptoms of serious infections
- make sure that you are vaccinated against serious infections caused by encapsulated bacteria and that you receive antibiotics if you need to start FABHALTA right away and you are not up to date on your vaccinations
- give you a Patient Safety Card about your risk of serious infections, as discussed above

For more information about side effects, see “What are the possible side effects of FABHALTA?”

What is FABHALTA?
FABHALTA is a prescription medicine used to:

- treat adults with a disease called paroxysmal nocturnal hemoglobinuria (PNH).
- reduce levels of protein in the urine (proteinuria) in adults with a kidney disease called primary immunoglobulin A nephropathy (IgAN), who are at risk of their disease progressing quickly.
- treat adults with a kidney disease called complement 3 glomerulopathy (C3G), to reduce levels of protein in the urine (proteinuria).

It is not known if FABHALTA is safe and effective in children with PNH, IgAN, or C3G.

Who should not take FABHALTA?
Do not take FABHALTA if you:

- are allergic to iptacopan or any of the ingredients in FABHALTA. See the end of this Medication Guide for a complete list of ingredients in FABHALTA.
- have a serious infection caused by encapsulated bacteria, including Streptococcus pneumoniae, Neisseria meningitidis, or Haemophilus influenzae type b when you are starting FABHALTA treatment.

Before you take FABHALTA, tell your healthcare provider about all of your medical conditions, including if you:

- have an infection or fever
- have liver problems
- are pregnant or plan to become pregnant. It is not known if FABHALTA will harm your unborn baby.
- are breastfeeding or plan to breastfeed. It is not known if FABHALTA passes into your breast milk. You should not breastfeed during treatment and for 5 days after your final dose of FABHALTA.

Tell your healthcare provider about all the medicines you take, including prescription and over-the-counter medicines, vitamins, and herbal supplements. Taking FABHALTA with certain other medicines may affect the way FABHALTA works and may cause side effects.
Know the medicines you take and the vaccines you receive. Keep a list of them to show your healthcare provider and pharmacist when you get a new medicine.

How should I take FABHALTA?

- Take FABHALTA exactly as your healthcare provider tells you. Do not change the dose or stop taking FABHALTA unless your healthcare provider tells you.
- Take 1 FABHALTA capsule 2 times each day, with or without food.
- Swallow the capsules whole. Do not open, break, or chew capsules.
- If you miss a dose or doses of FABHALTA, take 1 dose of FABHALTA as soon as you remember, even if it is almost time to take your next scheduled dose, and then take your next dose of FABHALTA at your regularly scheduled time.

For people with PNH:

- If you are changing treatment from eculizumab to FABHALTA, you should take your starting dose of FABHALTA no later than 1 week after your last dose of eculizumab.
- If you are changing treatment from ravulizumab to FABHALTA, you should take your starting dose of FABHALTA no later than 6 weeks after your last dose of ravulizumab.
- If you stop taking FABHALTA, your healthcare provider will need to monitor you closely for at least 2 weeks after stopping FABHALTA. Stopping treatment with FABHALTA may cause a breakdown of red blood cells due to PNH.

Symptoms or problems that can happen due to breakdown of red blood cells include:

○ decreased hemoglobin level in your blood
○ blood in your urine
○ shortness of breath
○ trouble swallowing

○ tiredness
○ pain in the stomach (abdomen)
○ blood clots, stroke, and heart attack
○ erectile dysfunction

- It is important you take FABHALTA exactly as your healthcare provider tells you to lower the possibility of breakdown of red blood cells due to PNH.

What are the possible side effects of FABHALTA?
FABHALTA may cause serious side effects, including:

- See “What is the most important information I should know about FABHALTA?”
- Increased cholesterol and triglyceride (lipid) levels in your blood. Your healthcare provider will do blood tests to check your cholesterol and triglycerides during treatment with FABHALTA. Your healthcare provider may start you on a medicine to lower your cholesterol if needed.

The most common side effects of FABHALTA in adults include:

- headache
- nasal congestion, runny nose, cough, sneezing, and sore throat (nasopharyngitis)
- diarrhea

- pain in the stomach (abdomen)
- infections (bacterial and viral)
- nausea
- rash

Tell your healthcare provider about any side effect that bothers you or that does not go away. These are not all of the possible side effects of FABHALTA.
Call your doctor for medical advice about side effects. You may report side effects to FDA at 1-800-FDA-1088.

How should I store FABHALTA?

- Store FABHALTA capsules at room temperature between 68°F to 77°F (20°C to 25°C).
- The FABHALTA container contains a child resistant cap.

Keep FABHALTA and all medicines out of the reach of children.

General information about the safe and effective use of FABHALTA.
Medicines are sometimes prescribed for purposes other than those listed in a Medication Guide. Do not use FABHALTA for a condition for which it was not prescribed. Do not give FABHALTA to other people, even if they have the same symptoms that you have. It may harm them. You can ask your pharmacist or healthcare provider for information about FABHALTA that is written for health professionals.

What are the ingredients in FABHALTA?
Active ingredient: iptacopan
Inactive ingredients: the capsule shell contains gelatin, red ferric oxide, titanium dioxide, yellow ferric oxide. The black printing ink contains ferrosoferric oxide, potassium hydroxide, propylene glycol, shellac, and strong ammonia solution.
Distributed by: Novartis Pharmaceuticals Corporation, East Hanover, New Jersey 07936
© Novartis
For more information, go to www.FABHALTA.com or call 1-888-669-6682.

This Medication Guide has been approved by the U.S. Food and Drug Administration.

Revised: March 2025

T2025-16

PRINCIPAL DISPLAY PANEL

NDC 0078-1189-20

Rx only

FABHALTA®
(iptacopan) capsules

200 mg

Dispense with accompanying Medication Guide.

60 capsules

Swallow the capsules whole. Do not open, break, or chew capsules.

NOVARTIS